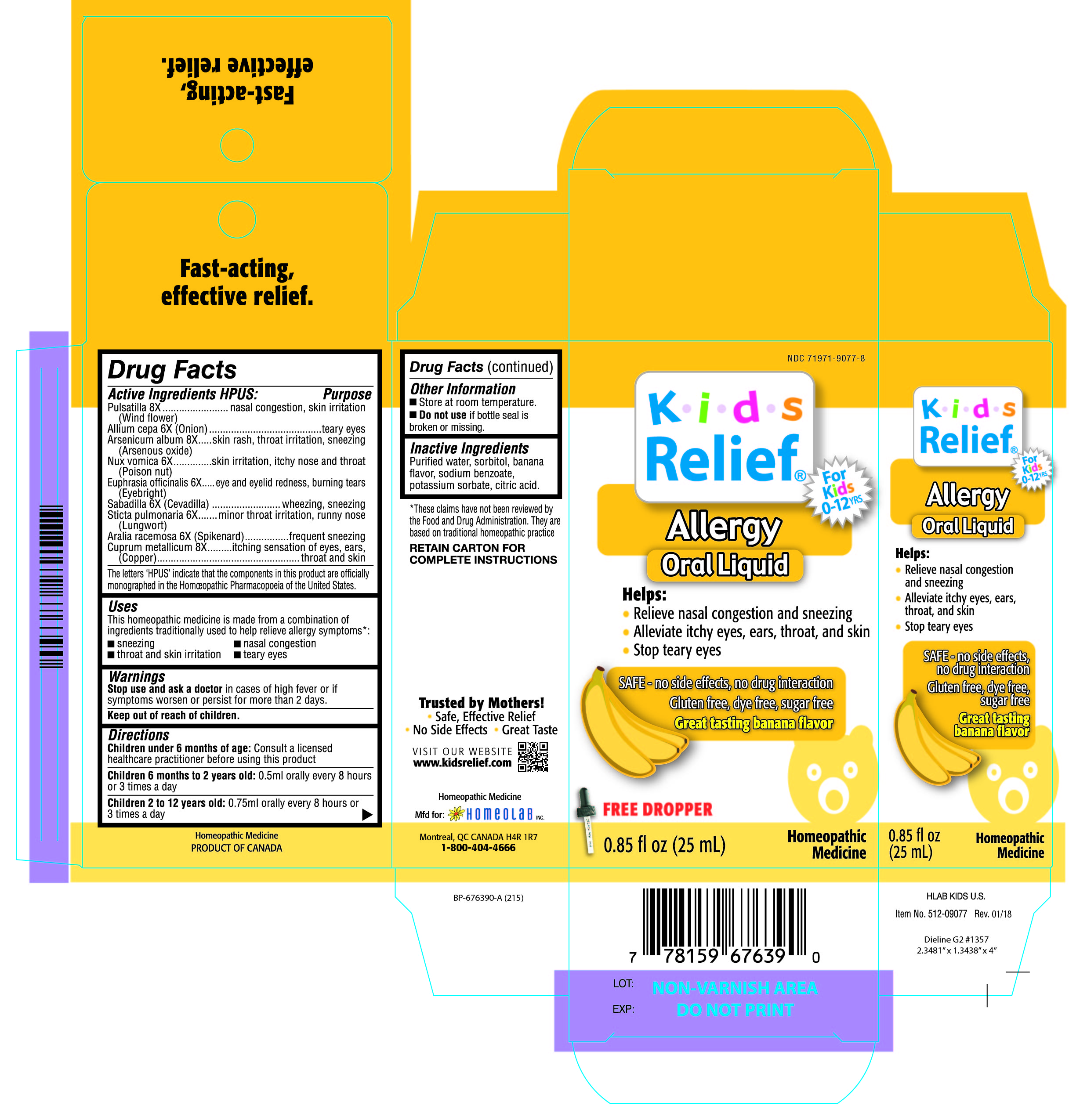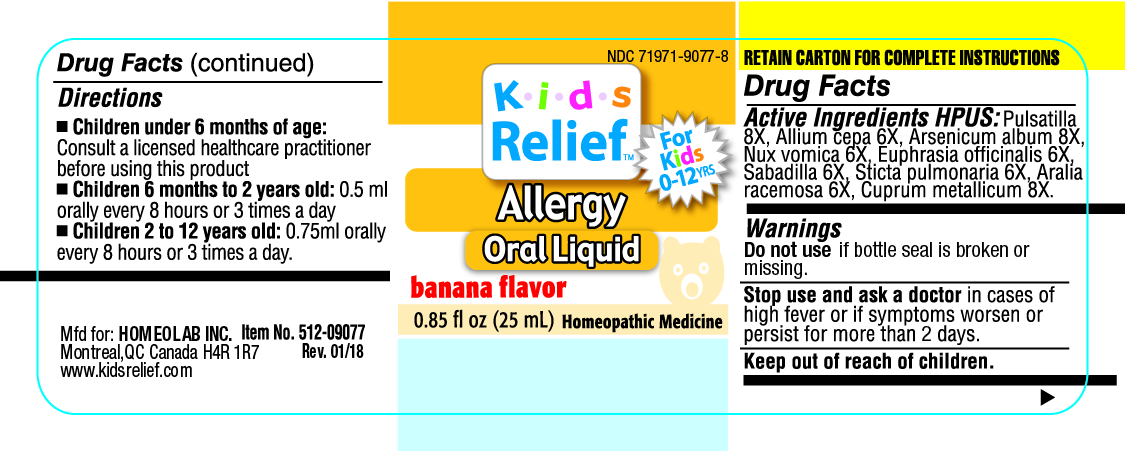 DRUG LABEL: Kids Relief
NDC: 71971-9077 | Form: LIQUID
Manufacturer: Homeolab International (Canada) inc
Category: homeopathic | Type: HUMAN OTC DRUG LABEL
Date: 20190716

ACTIVE INGREDIENTS: ANEMONE PULSATILLA 8 [hp_X]/25 mL; ONION 6 [hp_X]/25 mL; ARSENIC TRIOXIDE 8 [hp_X]/25 mL; STRYCHNOS NUX-VOMICA SEED 6 [hp_X]/25 mL; EUPHRASIA STRICTA 6 [hp_X]/25 mL; SCHOENOCAULON OFFICINALE SEED 6 [hp_X]/25 mL; LOBARIA PULMONARIA 6 [hp_X]/25 mL; ARALIA RACEMOSA ROOT 6 [hp_X]/25 mL; COPPER 8 [hp_X]/25 mL
INACTIVE INGREDIENTS: WATER; SORBITOL; SODIUM BENZOATE; POTASSIUM SORBATE; CITRIC ACID ACETATE

Active Ingredients HPUS:

Pulsatilla 8X

(Wind flower)

Allium cepa 6X (Onion)

Arsenicum album 8X

(Arsenous oxide)

Nux Vomica 6X

(Poison nut)

Euphrasia officinalis 6X

(Eyebright)

Sabadilla 6X (Cevadilla)

Sticta pulmonaria 6X

(Lungwort)

Aralia racemosa 6X (Spikenard)

Cuprum metallicum 8X

(Copper)

The letters 'HPUS' indicate that the component in this product is officially

monographed in the Homeopathic Pharmacopoeia of the United States.

Purpose

Pulsatilla 8X......................................nasal congestion, skin irritation

(Wind flower)

Allium cepa 6X (Onion)......................teary eyes

Arsenicum album 8X..........................skin rash, throat irritation, sneezing

(Arsenous oxide)

Nux Vomica 6X..................................skin irritation, itchy nose and throat

(Poison nut)

Euphrasia officinalis 6X.......................eye and eyelid redness, burning tears

(Eyebright)

Sabadilla 6X (Cevadilla)......................wheezing, sneezing

Sticta pulmonaria 6X...........................minor thorat irritation, runny nose

(Lungwort)

Aralia racemosa 6X (Spikenard)............frequent sneezing

Cuprum metallicum 8X........................itching sensation of eyes, ears, throat and skin

(Copper)

Uses

This homeopathic medicine is made from a combination of

ingredients traditionally used to help relieve allergy symptoms*:

•sneezing •nasal congestion

•throat and skin irritation •teary eyes

Warnings

Stop use and ask a doctor in cases of hgh fever or if

symptoms worsen or persist for more than 2 days.

Keep out of reach of children.

Directions

Children under 6 months of age: Consult a licensed healthcare

practitioner before using this product

Children under 6 months to 2 years old: 0.5 ml orally every 8 hours

or 3 times a day

Children 2 to 12 years old: 0.75 ml orally every 8 hours or

3 times a day

Other information

•Store at room temperature

•Do not use if bottle seal

is broken or missing.

Inactive Ingredients

Purified water, sorbitol, banana

flavor, sodium benzoate,

potassium sorbate, citric acid.